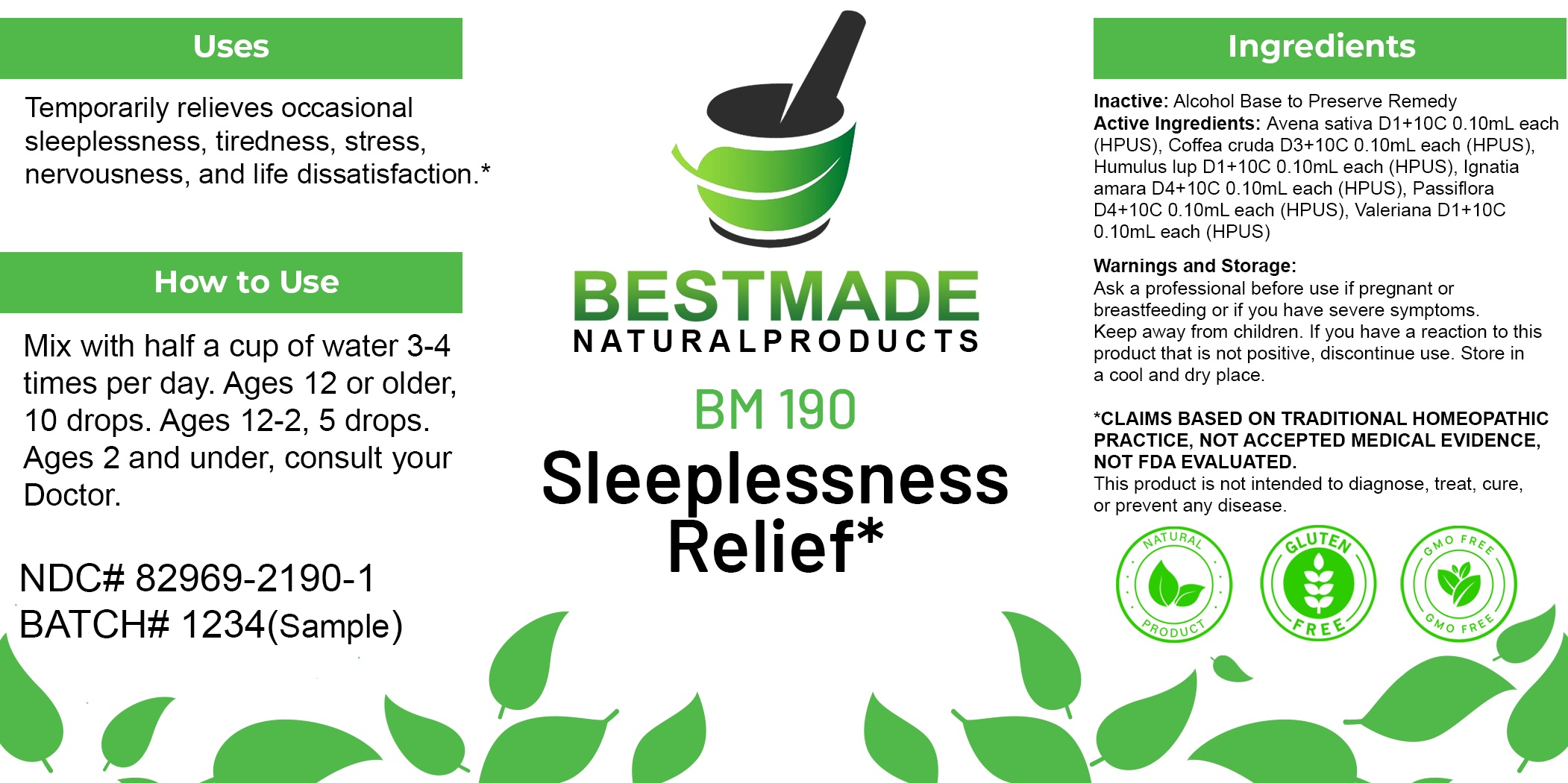 DRUG LABEL: Bestmade Natural Products BM190
NDC: 82969-2190 | Form: LIQUID
Manufacturer: Bestmade Natural Products
Category: homeopathic | Type: HUMAN OTC DRUG LABEL
Date: 20250221

ACTIVE INGREDIENTS: ARABICA COFFEE BEAN 30 [hp_C]/30 [hp_C]; STRYCHNOS IGNATII SEED 30 [hp_C]/30 [hp_C]; AVENA SATIVA FLOWERING TOP 30 [hp_C]/30 [hp_C]; VALERIAN 30 [hp_C]/30 [hp_C]; HOPS 30 [hp_C]/30 [hp_C]; PASSIFLORA INCARNATA FLOWERING TOP 30 [hp_C]/30 [hp_C]
INACTIVE INGREDIENTS: ALCOHOL 30 [hp_C]/30 [hp_C]

BM190

DOSAGE AND ADMINISTRATION

How to Use

Mix with half a cup of water 3-4 times per day. Ages 12 or older, 10 drops. Ages 12-2, 5 drops. Ages 2 and under, consult your Doctor.

Inactive:

Alcohol Base to Preserve Product

ACTIVE INGREDIENT

Active Ingredients: Avena sativa D1+10C 0.10mL each (HPUS), Coffea cruda D3+10C 0.10mL each (HPUS), Humulus lup D1+10C 0.10mL each (HPUS), Ignatia amara D4+10C 0.10mL each (HPUS), Passiflora D4+10C 0.10mL each (HPUS), Valeriana D1+10C 0.10mL each (HPUS)

KEEP OUT OF REACH OF CHILDREN

Warnings and Storage:

Ask a professional before use if pregnant or breastfeeding or if you have severe symptoms.

Keep away from children. If you have a reaction to this product that is not positive, discontinue use. Store in a cool and dry place

*CLAIMS BASED ON TRADITIONAL HOMEOPATHIC PRACTICE, NOT ACCEPTED MEDICAL EVIDENCE NOT FDA EVALUATED.
This product is not intended to diagnose, treat, cure, or prevent any disease.

Warnings and Storage:

Ask a professional before use if pregnant or breastfeeding or if you have severe symptoms.

Keep away from children. If you have a reaction to this product that is not positive, discontinue use. Store in a cool and dry place

*CLAIMS BASED ON TRADITIONAL HOMEOPATHIC PRACTICE, NOT ACCEPTED MEDICAL EVIDENCE NOT FDA EVALUATED.
This product is not intended to diagnose, treat, cure, or prevent any disease.

Uses
Temporarily relieves occasional sleeplessness, tiredness, stress, nervousness, and life dissatisfaction.*

Uses
Temporarily relieves occasional sleeplessness, tiredness, stress, nervousness, and life dissatisfaction.*

Entire package label